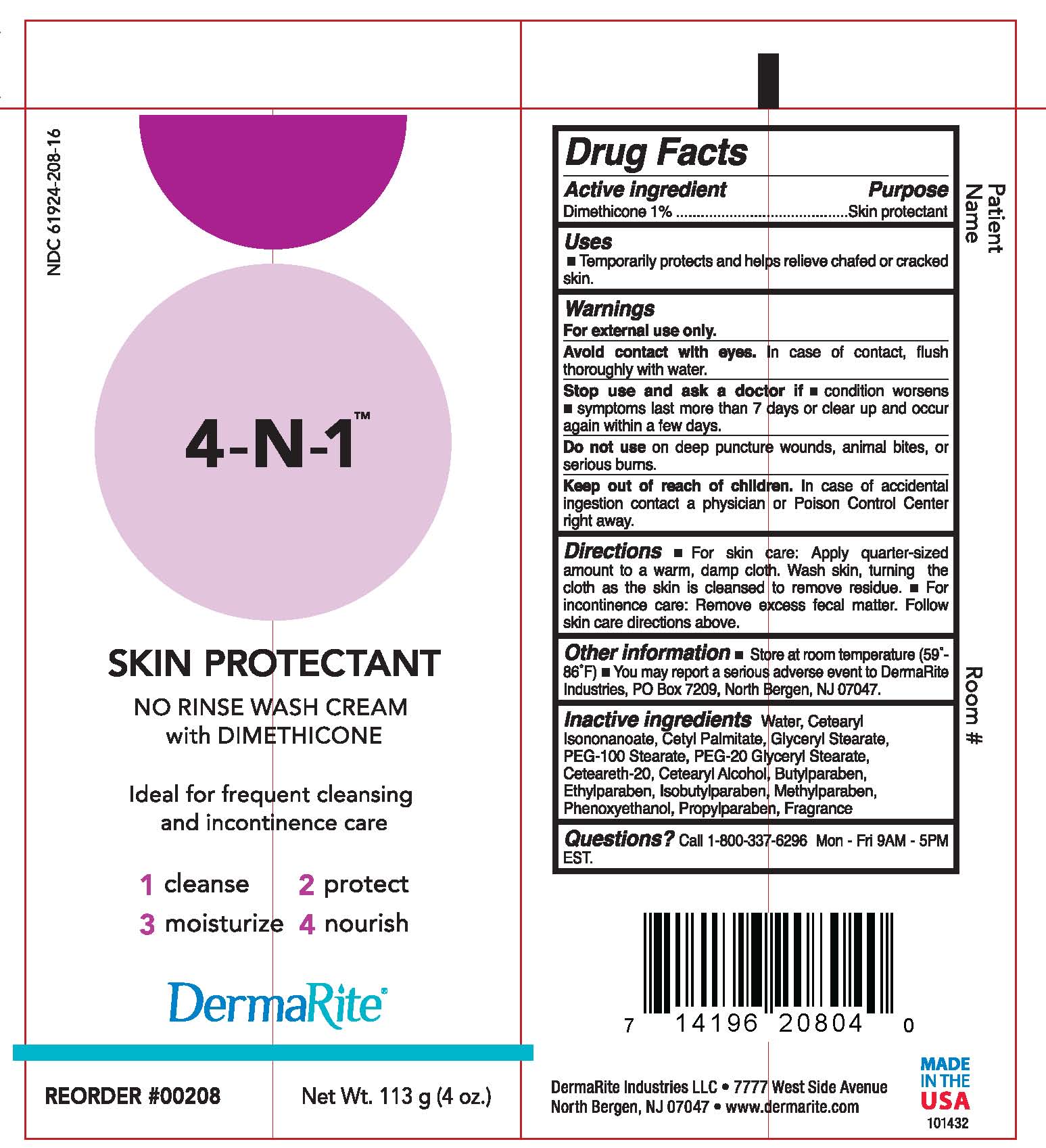 DRUG LABEL: 4-N-1 WASH
NDC: 61924-208 | Form: CREAM
Manufacturer: DermaRite Industries, LLC
Category: otc | Type: HUMAN OTC DRUG LABEL
Date: 20241205

ACTIVE INGREDIENTS: DIMETHICONE 0.01 g/1 g
INACTIVE INGREDIENTS: WATER; GLYCERYL MONOSTEARATE; PEG-100 STEARATE; CETEARYL ISONONANOATE; CETYL PALMITATE; CETOSTEARYL ALCOHOL; PEG-20 GLYCERYL STEARATE; POLYOXYL 20 CETOSTEARYL ETHER; PHENOXYETHANOL; METHYLPARABEN; BUTYLPARABEN; ETHYLPARABEN; PROPYLPARABEN; ISOBUTYLPARABEN

DRUG LISTING: 4-N-1 WASH CREAM

Active Ingredients:

Dimethicone 1%

Purpose:

Skin Protectant

Uses:

- A gentle alternative to soap and water.
- Cleans, restores, nourishes, and protects even most delicate skin.
- Ideal for frequent cleansing and incontinence care.

Warnings:

- For external use only.
- Avoid contact with eyes. In case of contact, flush thoroughly with water.
- Stop use and ask a doctor if – condition worsens or does not improve within 7 days; symptoms clear up and occur again within a few days.
- Do not use on deep puncture wounds, animal bites, or serious burns.

Warnings:

- Keep out of reach of children. In case of accidental ingestion contact a physician or Poison Control Center right away.

Directions:

- For skin care: Apply quarter-sized amount to warm, damp cloth. Wash skin, turning the cloth as the skin is cleansed to remove residue.
- For incontinence care: Remove excess fecal matter. Follow skin care directions above

Other Information:

Store at room temperature (59°-86°F)

Ingredients:

Butylparaben, Ceteareth-20, Cetearyl Alcohol, Cetearyl Isononanoate, Cetyl Palmitate, Ehtylparaben, Fragrance, Glyceryl Stearate, Isobutylparaben, Methyl paraben, PEG-100 Stearate, PEG-20 Glyceryl Stearate, Phenoxyethanol, Propylparaben, Water